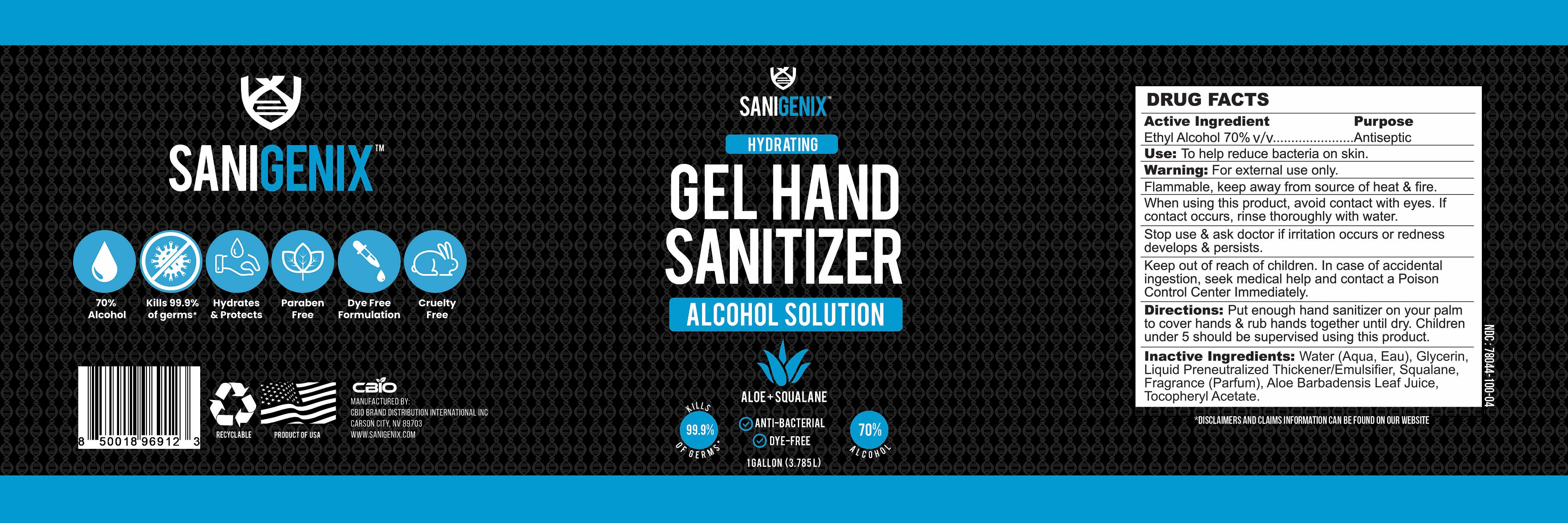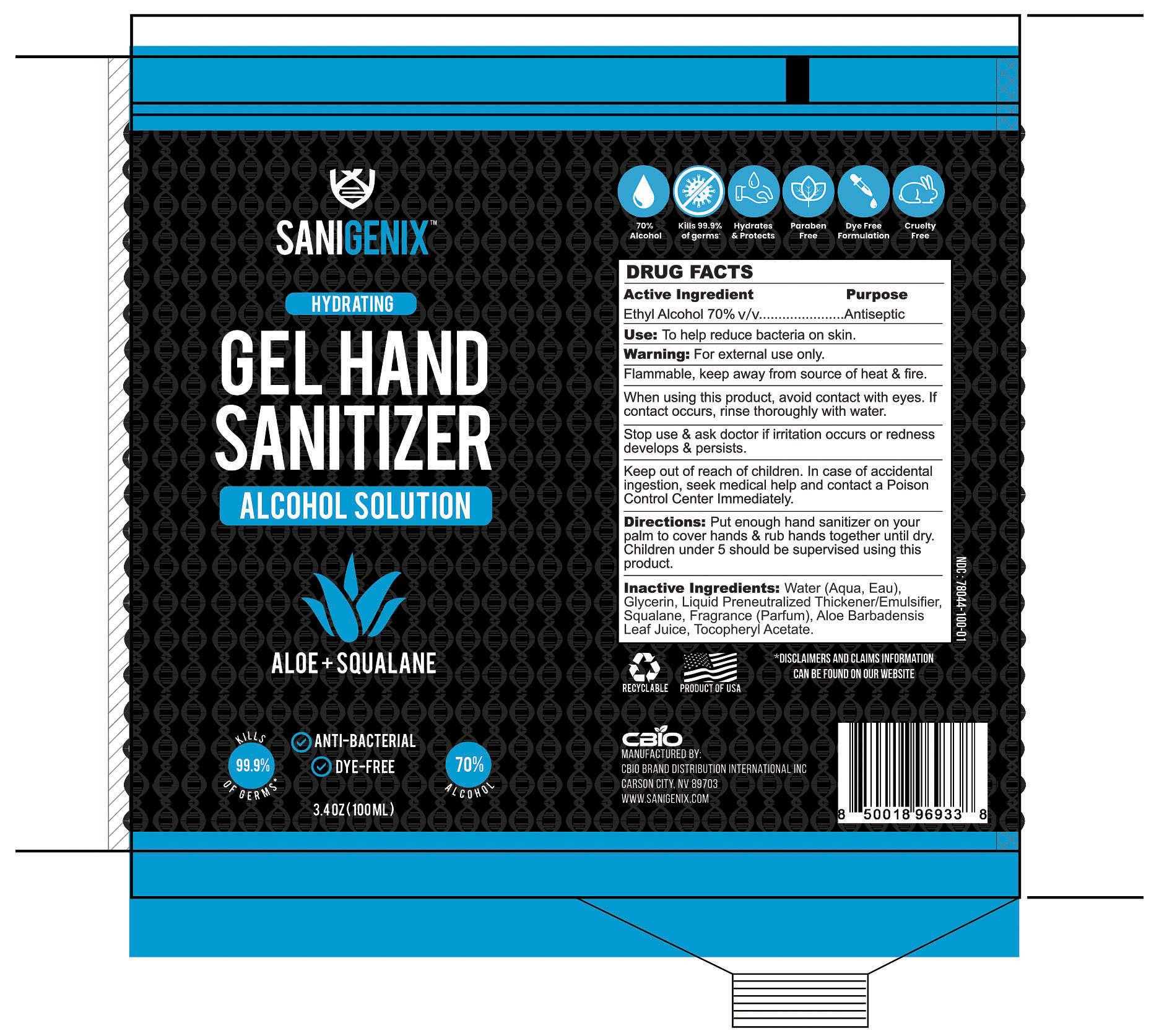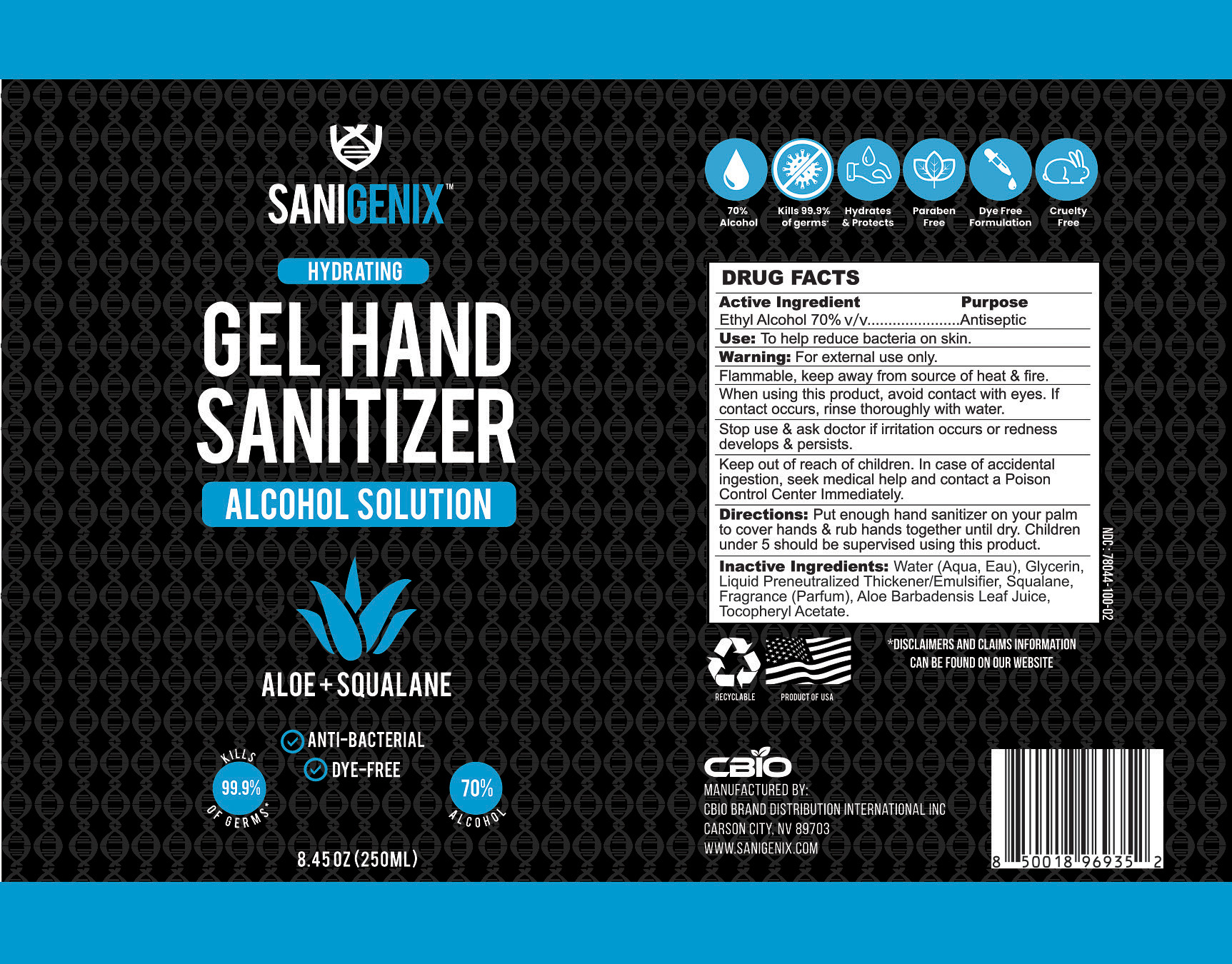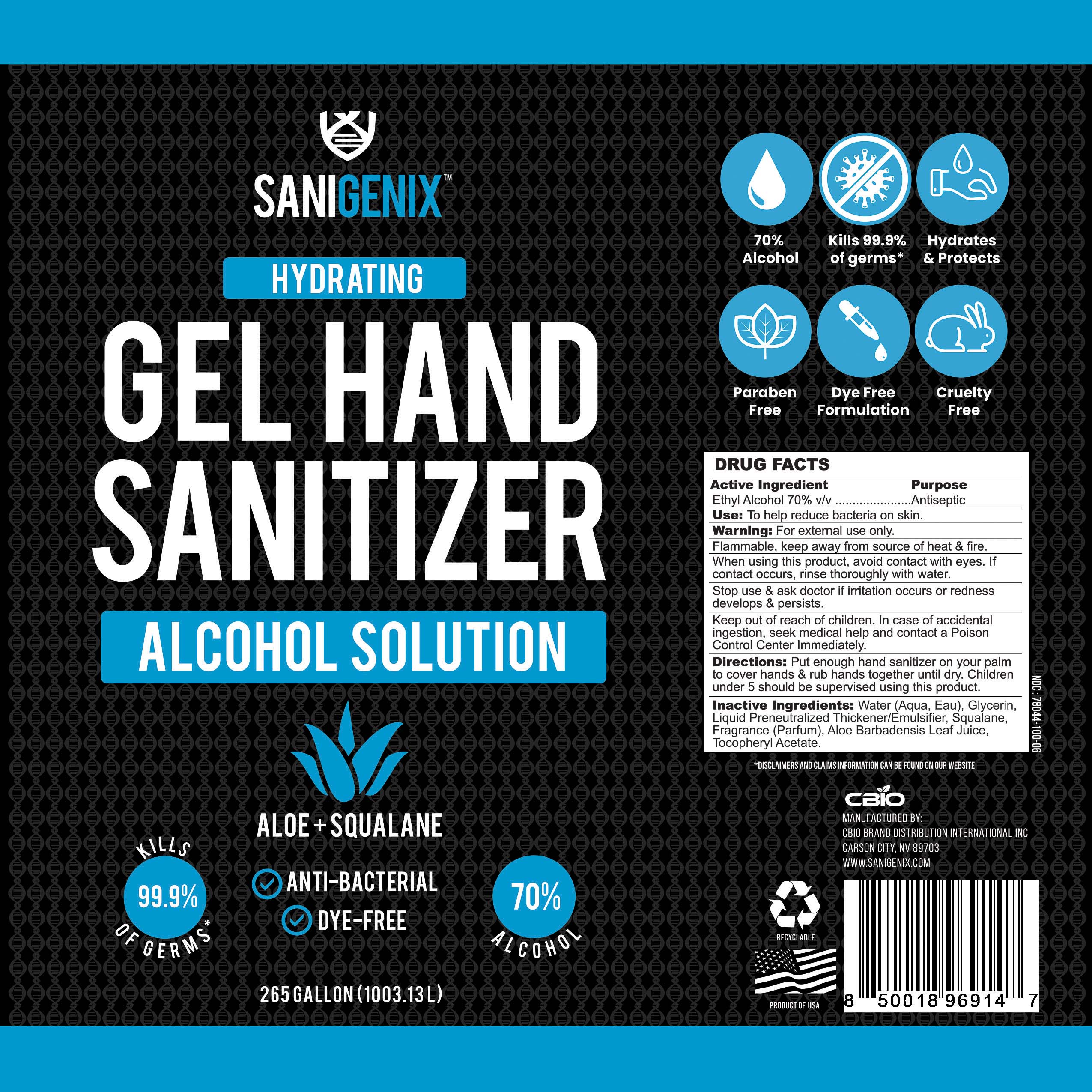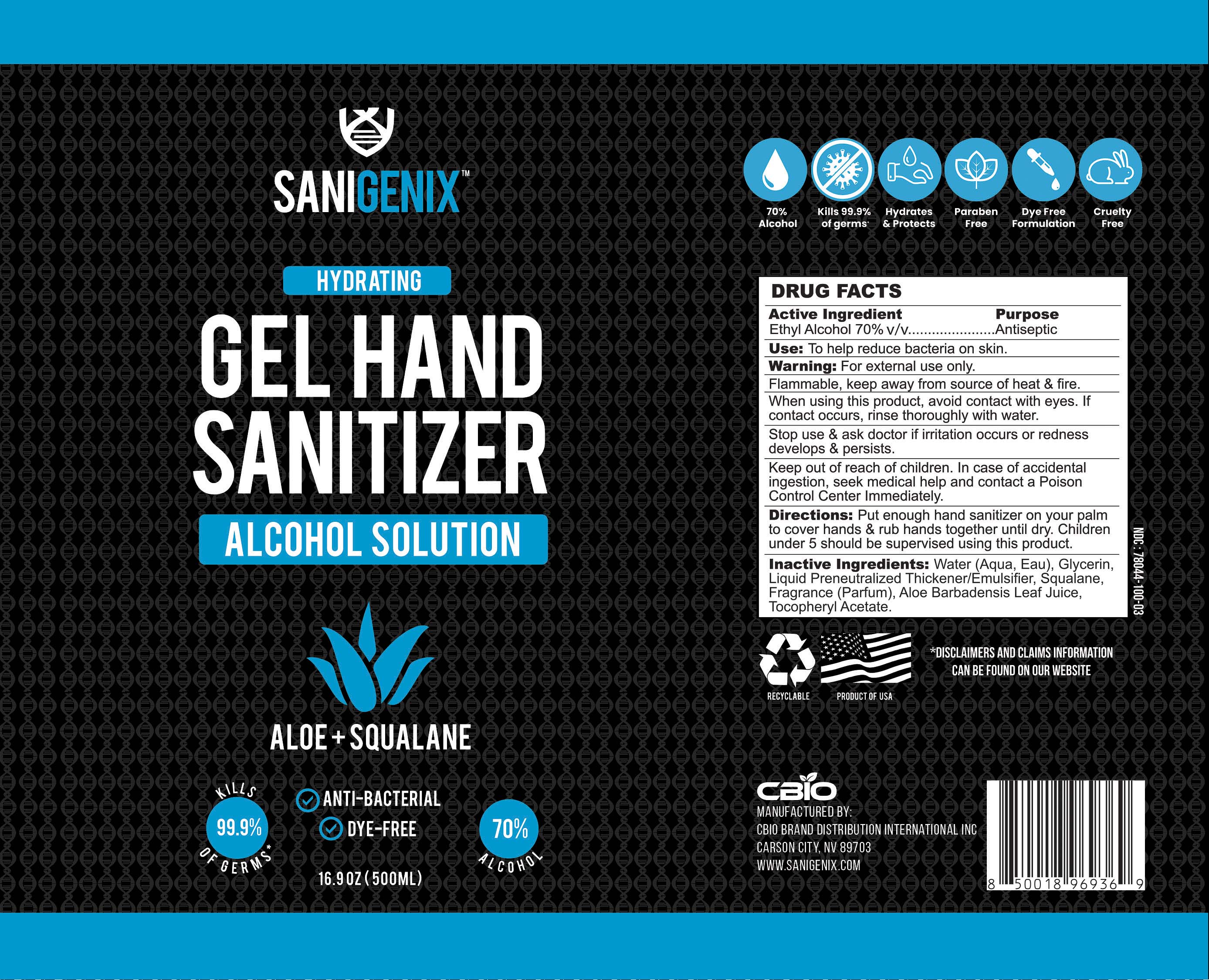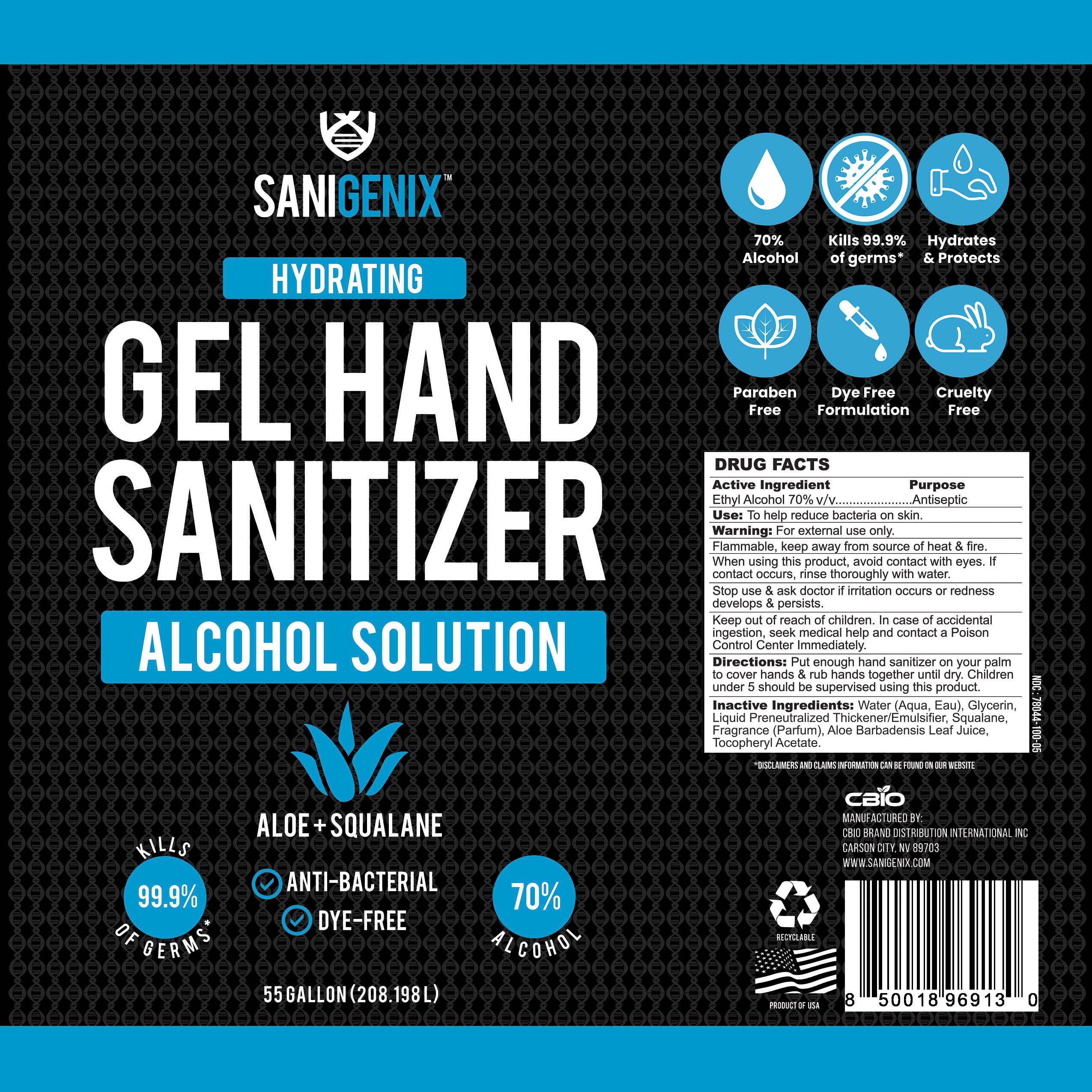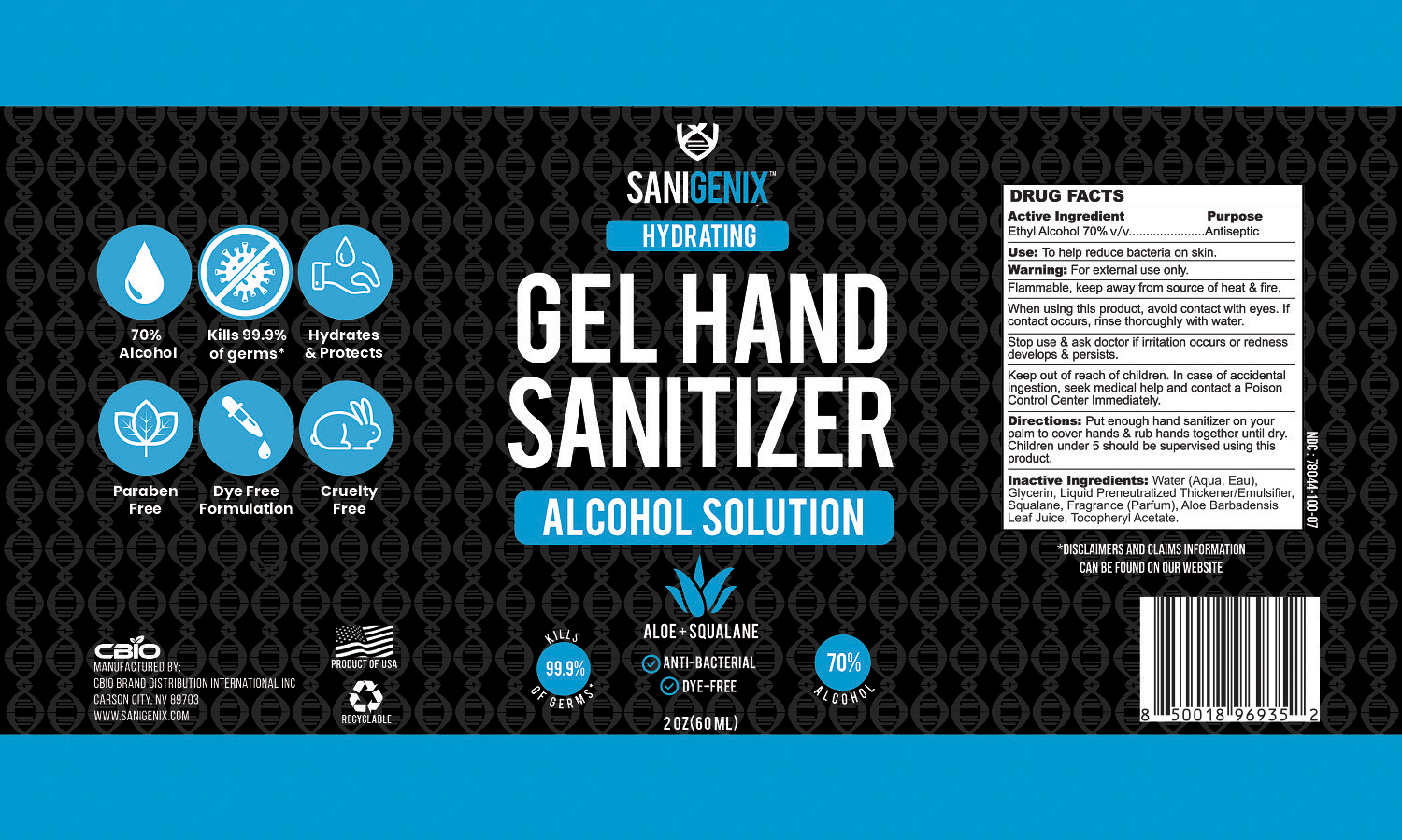 DRUG LABEL: 70% Gel Hand Sanitizer
NDC: 78044-100 | Form: GEL
Manufacturer: CBIO Brand Distribution International Inc.
Category: otc | Type: HUMAN OTC DRUG LABEL
Date: 20200611

ACTIVE INGREDIENTS: ALCOHOL 70 mL/100 mL
INACTIVE INGREDIENTS: GLYCERIN 1.45 mL/100 mL; .ALPHA.-TOCOPHEROL ACETATE, D-; WATER; RAPIDGEL EZ1; SQUALANE; ALOE VERA LEAF

Active Ingredient(s)

Ethyl Alcohol 70% v/v. Purpose: Antiseptic

Purpose

Antiseptic, Hand Sanitizer

Use

To help reduce bacteria on skin.

Warnings

For external use only. Flammable, keep away from source of heat & fire.

When using this product, avoid contact with eyes. If contact occurs, rinse thoroughly with water.

Stop use & ask doctor if irritation occurs or redness develops & persists.

Keep out of reach of children. In case of accidental ingestion, seek medical help and contact a Poison Control Center Immediately.

Directions

Put enough hand sanitizer on your palm to cover hands & rub hands together until dry. Children under 5 should be supervised using this product.

Inactive ingredients

Water (Aqua, Eau), Glycerin, Liquid Preneutralized Thickener/Emulsifier, Squalane, Fragrance (Parfum), Aloe Barbadensis Leaf Juice, Tocopheryl Acetate.

RECENT MAJOR CHANGES

Section 3:

To help reduce bacteria on skin. (06/2020)

Section 8:

Put enough hand sanitizer on your palm to cover hands & rub hands together until dry. Children under 5 should be supervised using this product. (06/2020)

Package Label - Principal Display Panel

60 mL NDC: 78044-100-07

100 mL NDC: 78044-100-01

250 mL NDC: 78044-100-02

500 mL NDC: 78044-100-03

3.785 L NDC: 78044-100-04

208.198 L NDC: 78044-100-05

1003.13 L NDC: 78044-100-06